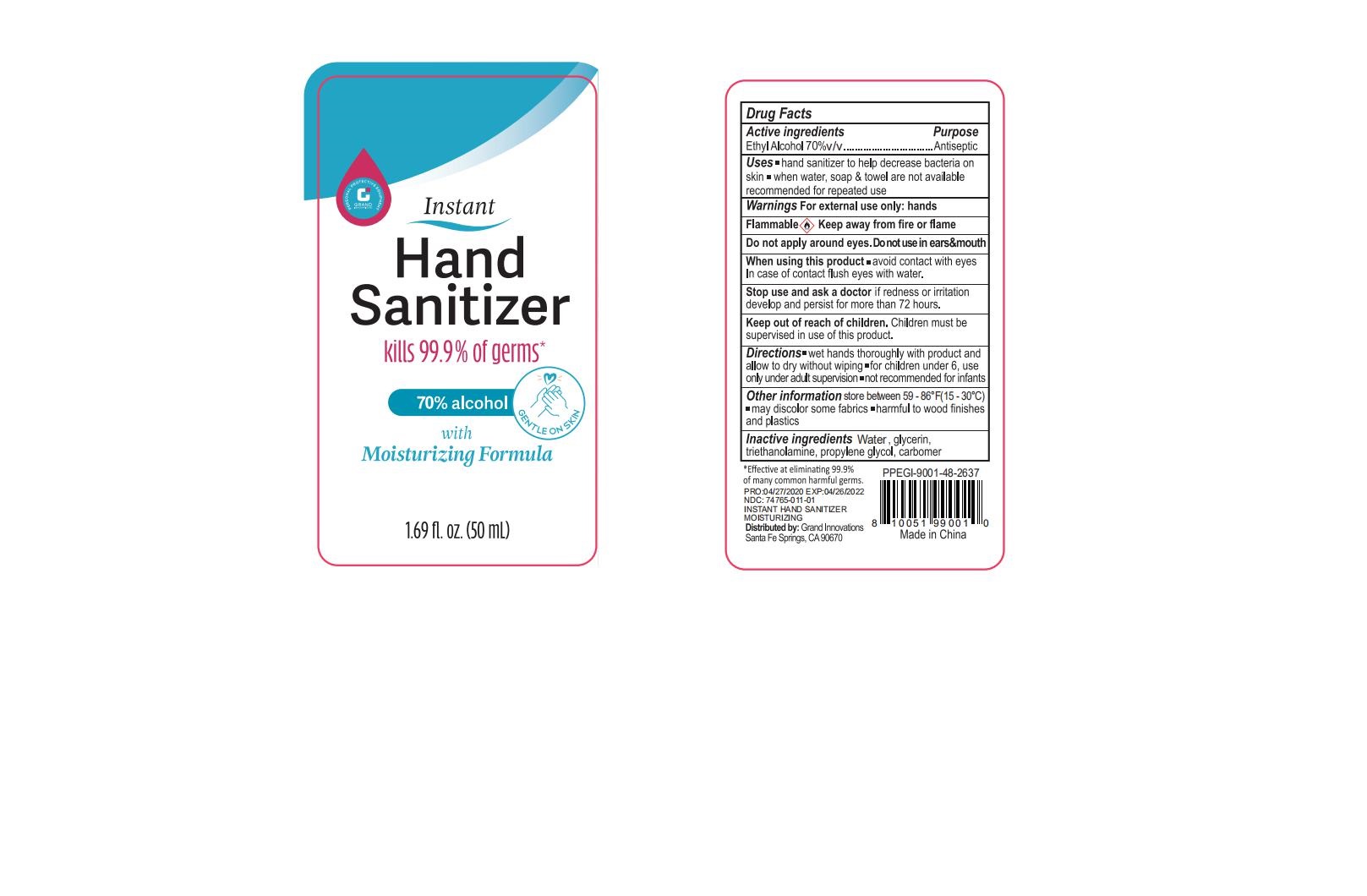 DRUG LABEL: GRAND INNOVATIONS Hand Sanitizer
NDC: 74765-011 | Form: GEL
Manufacturer: Zhejiang Yiwu Limei Cosmetics Co., Ltd
Category: otc | Type: HUMAN OTC DRUG LABEL
Date: 20200505

ACTIVE INGREDIENTS: ALCOHOL 70 mL/100 mL
INACTIVE INGREDIENTS: PROPYLENE GLYCOL; CARBOMER 980; GLYCERIN; TROLAMINE; WATER

NA

Active Ingredient(s)

Ethyl Alcohol 70% v/v. Purpose: Antiseptic

Purpose

Antiseptic, Hand Sanitizer

Use

Hand Sanitizer to help decrease bacteria on skin. when water, soap& towel are not available. recommended for repeated use.

Warnings

For external use only: hands. Flammable. Keep away from fire or flame

Do not use

- Do not apply around eyes.Do not use in ears&mouth

When using this product avoid contact with eyes, In case of contact flush eyes with water.
Stop use and ask a doctor if redness or irritation develop and persist for more than 72 hours.
Keep out of reach of children. Children must be supervised in use of this product.

Stop use and ask a doctor if redness or irritation develop and persist for more than 72 hours

Keep out of reach of children. Children must be supervised in use of this product.

Directions

wet hands thoroughly with product and allow to dry without wiping for children under 6, use only under adult supervision,
not recommended for infants

Other information

store between 59-86F (15~30C) ,may discolor some fabrics， harmful to wood finishes and plastics

Inactive ingredients

water, propylene glycol,glycerin, carbomer.triethanolamine

Package Label - Principal Display Panel

50 mL NDC: 74765-011-01

150 mL NDC: 74765-011-02

236 mL NDC: 74765-011-03

500 mL NDC: 74765-011-04